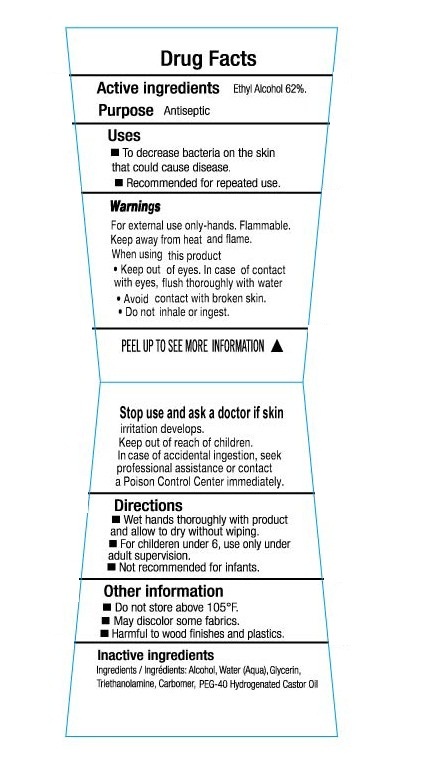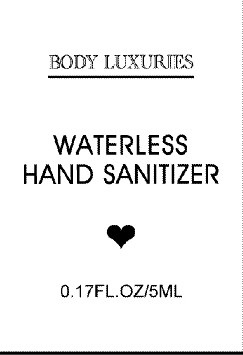 DRUG LABEL: Body Luxuries Waterless Hand Sanitizer
NDC: 50563-153 | Form: LIQUID
Manufacturer: Enchante Accessories
Category: otc | Type: HUMAN OTC DRUG LABEL
Date: 20100621

ACTIVE INGREDIENTS: ALCOHOL 62 mL/100 mL
INACTIVE INGREDIENTS: WATER; GLYCERIN; TROLAMINE; POLYOXYL 40 HYDROGENATED CASTOR OIL

BODY LUXURIES WATERLESS HAND SANITIZER

DRUG FACTS

Active Ingredients Purpose

Ethyl Alcohol 62% Antiseptic

Uses

To decrease bacteria on the skin that could cause disease

Recommended for repeated use.

Warnings:

For external use only-hands.

Flammable

Keep away from heat and flame.

When using this product

Keep out of eyes. In case of contact with eyes, flush thoroughly with water

Avoid contact with broken skin

Do not inhale or ingest

PEEL UP TO SEE MORE INFORMATON

Stop use and ask a doctor if skin irritation develops.

Keep out of reach of children.

In case of accidental ingestion, seek professional assistance or contact a poison control center immediately

Directions

Wet hands thoroughly with product and allow to dry without wiping

For children under 6, use only under adult supervision

Not recommended for infants.

Other information

Do not store above 105 degrees F

May discolor some fabrics

Harmful to wood finishes and plastics.

Inactive ingredients

Ingredients/Ingredients: Alcohol, Water (aqua), Glycerin

Triethanolamine, Carbomer, PEG-40 Hydrogenated Castor Oil

PACKAGE LABEL

BODY LUXURIES

WATERLESS HAND SANITIZERS

0.17 FL OZ/5ML